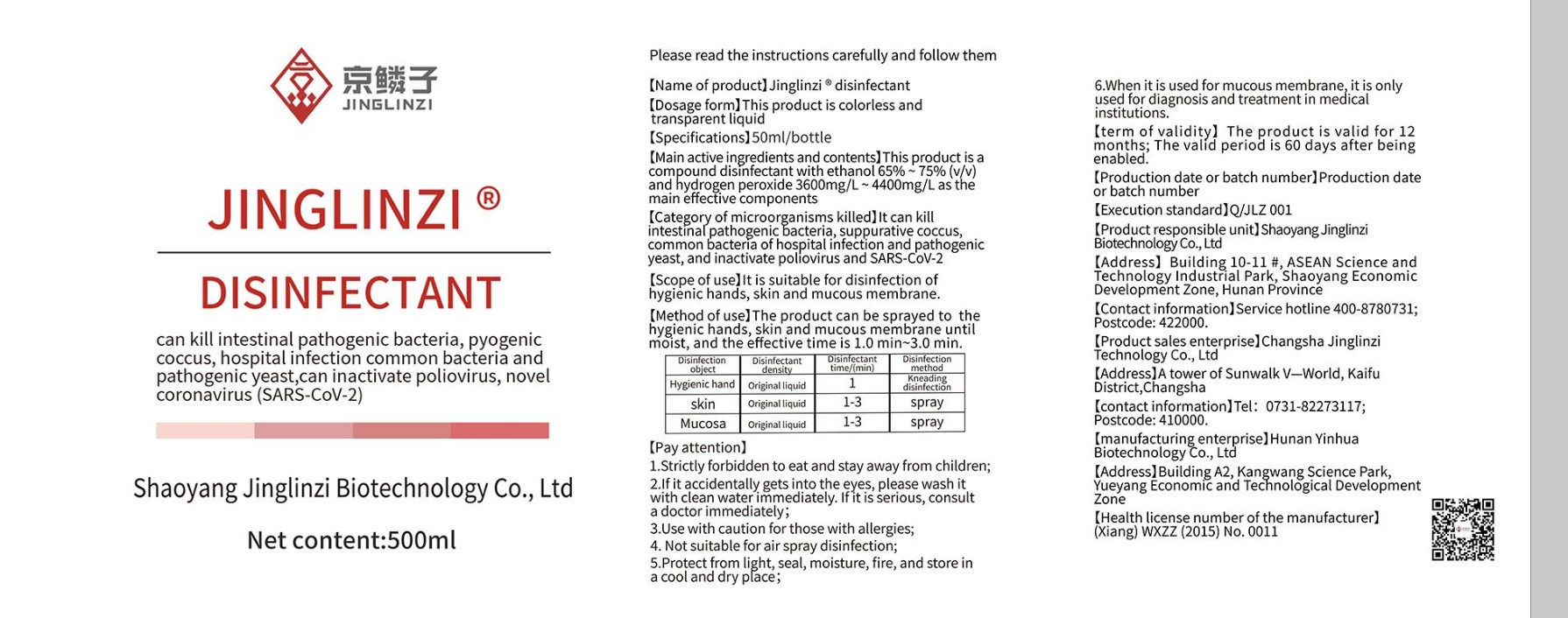 DRUG LABEL: Jinglinzi ethanol disinfectant
NDC: 83179-001 | Form: LIQUID
Manufacturer: Shaoyang Jinglinzi Biotechnology Co., Ltd
Category: otc | Type: HUMAN OTC DRUG LABEL
Date: 20230213

ACTIVE INGREDIENTS: HYDROGEN PEROXIDE 400 mg/100 mL; ALCOHOL 70 mL/100 mL
INACTIVE INGREDIENTS: WATER 30 mL/100 mL

Jinglinzi ethanol disinfectant

ACTIVE INGREDIENT

ethanol 65%-75% v/v. Purpose: Antiseptic

hydrogen peroxide 3600mg/L-4400mg/L Purpose: Antiseptic

PURPOSE

Antiseptic, Hand Sanitizer

INDICATIONS AND USAGE

Hand Sanitizer to help reduce bacteria that potentially can cause disease. For use when soap and water are not available.It can kill intestinal pathogenic bacteria, suppurative coccus, common bacteria of hospital infection and phthogeic yeast, and inactivate poliovirus and SARS-CoV-2

WARNINGS

For external use only. Flammable. Keep away from heat or flame

DO NOT USE

in children less than 2 months of age
on open skin wounds

When using this product keep out of eyes, ears, and mouth. In case of contact with eyes, rinse eyes thoroughly with water.
Stop use and ask a doctor if irritation or rash occurs. These may be signs of a serious condition.
Keep out of reach of children. If swallowed, get medical help or contact a Poison Control Center right away.

Stop use and ask a doctor if irritation or rash occurs. These may be signs of a serious condition.

Keep out of reach of children. If swallowed, get medical help or contact a Poison Control Center right away.

DOSAGE AND ADMINISTRATION

Place enough product on hands to cover all surfaces. Rub hands together until dry.
Supervise children under 6 years of age when using this product to avoid swallowing.

STORAGE AND HANDLING

Protect from light, seal, moisture, fire, and store in a cool and dry place

INACTIVE INGREDIENT

water

PACKAGE LABEL

500 mL NDC: 83179-001-01